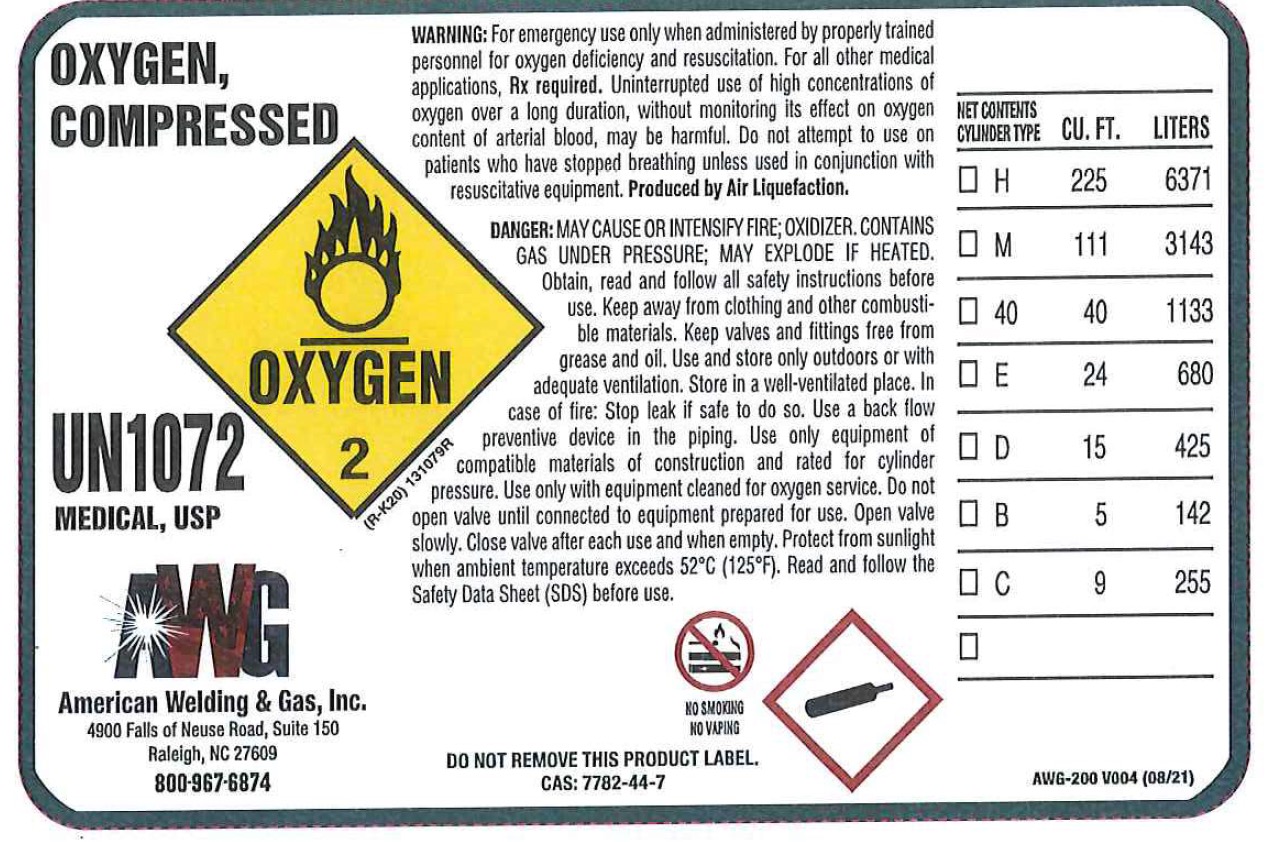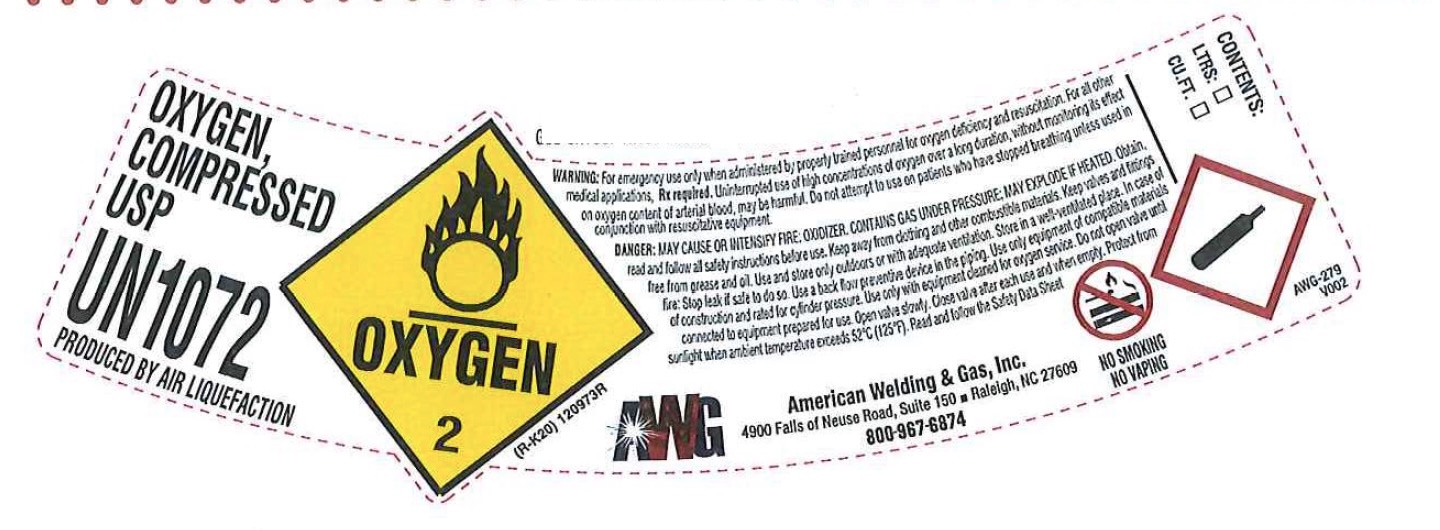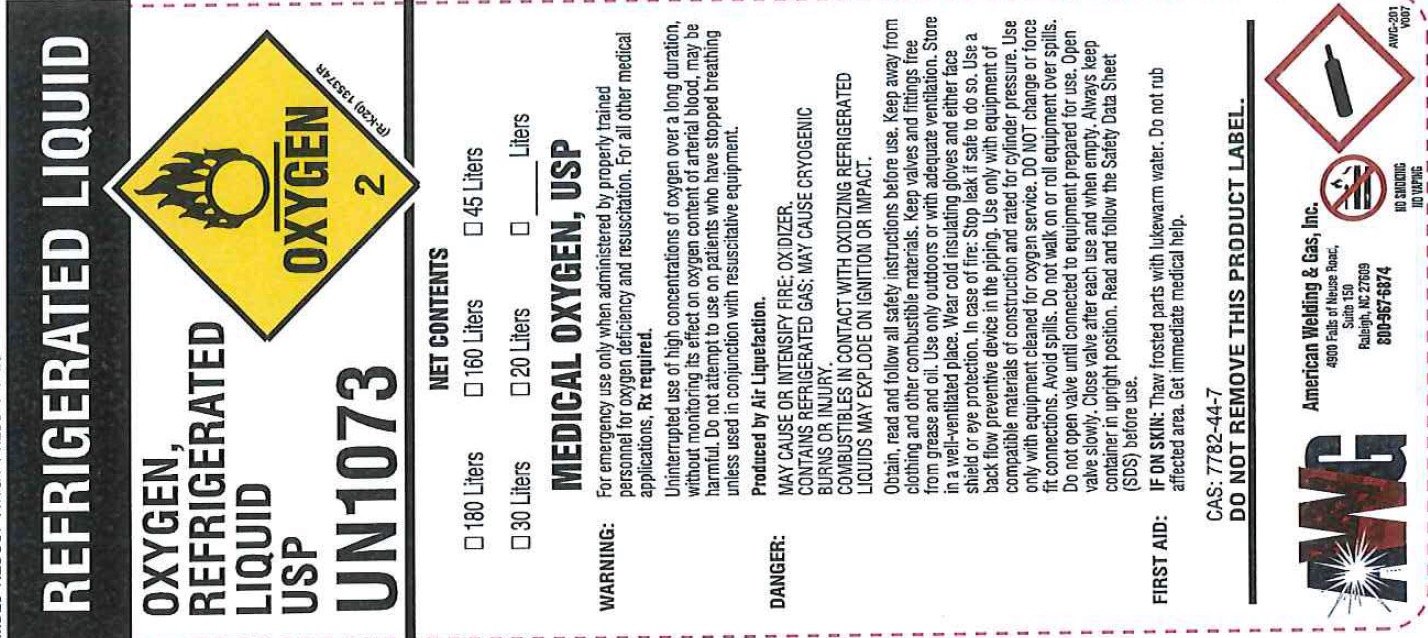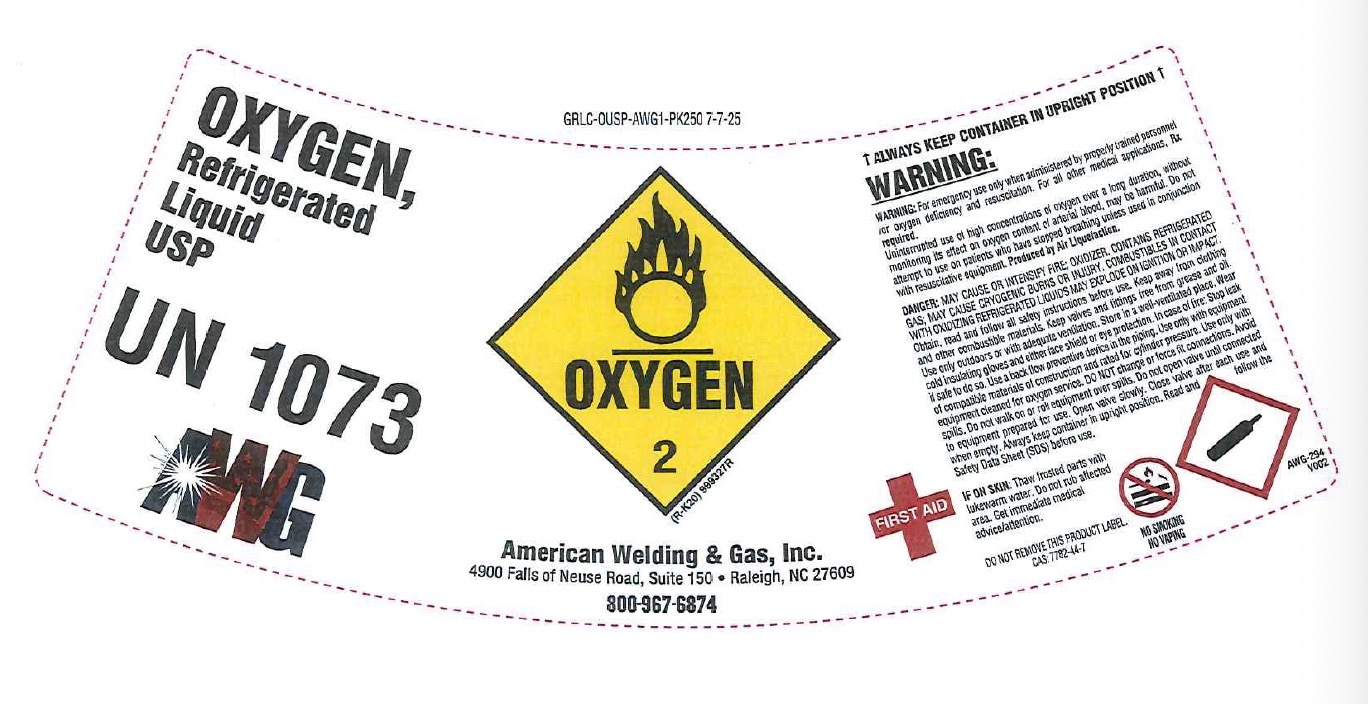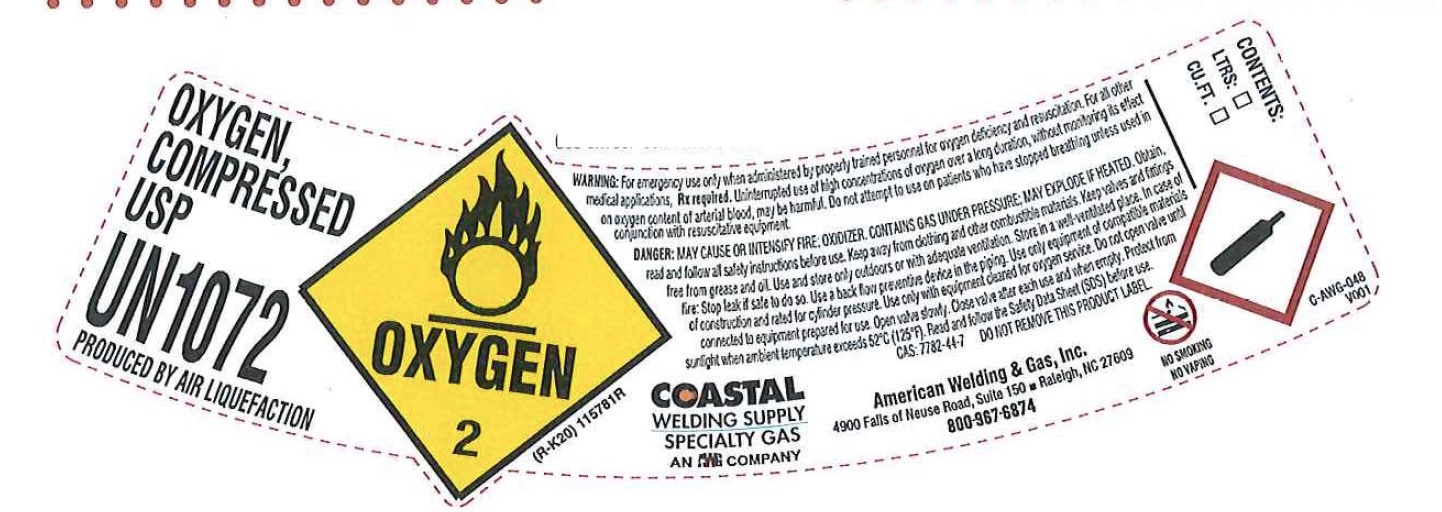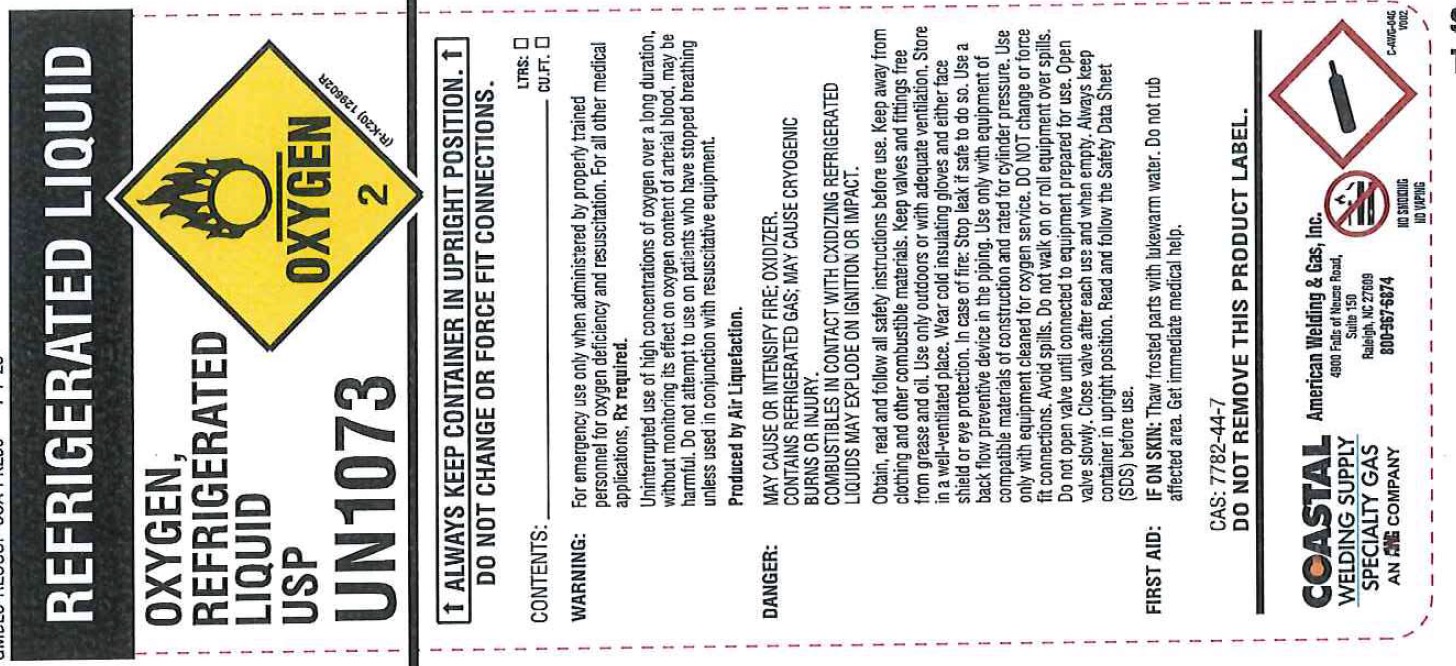 DRUG LABEL: Oxygen
NDC: 44076-010 | Form: GAS
Manufacturer: American Welding & Gas, Inc.
Category: prescription | Type: HUMAN PRESCRIPTION DRUG LABEL
Date: 20251028

ACTIVE INGREDIENTS: OXYGEN 990 mL/1 L

Oxygen

PACKAGE LABEL

OXYGEN, COMPRESSED – MEDICAL, USP – UN1072

WARNING:
For emergency use only when administered by properly trained personnel for oxygen deficiency and resuscitation. For all other medical applications, Rx required. Uninterrupted use of high concentrations of oxygen over a long duration, without monitoring its effect on oxygen content of arterial blood, may be harmful. Do not attempt to use on patients who have stopped breathing unless used in conjunction with resuscitative equipment.
Produced by Air Liquefaction.

DANGER:
MAY CAUSE OR INTENSIFY FIRE; OXIDIZER. CONTAINS GAS UNDER PRESSURE; MAY EXPLODE IF HEATED.
Obtain, read and follow all safety instructions before use. Keep away from clothing and other combustible materials. Keep valves and fittings free from grease and oil. Use and store only outdoors or with adequate ventilation. Store in a well-ventilated place. In case of fire: Stop leak if safe to do so. Use a back flow preventive device in the piping. Use only equipment of compatible materials of construction and rated for cylinder pressure. Use only with equipment cleaned for oxygen service. Do not open valve until connected to equipment prepared for use. Open valve slowly. Close valve after each use and when empty. Protect from sunlight when ambient temperature exceeds 52C (125F). Read and follow the Safety Data Sheet (SDS) before use.

NO SMOKING
NO VAPING

American Welding & Gas, Inc.
4900 Falls of Neuse Road, Suite 150
Raleigh, NC 27609
800-967-6874

DO NOT REMOVE THIS PRODUCT LABEL.
CAS: 7782-44-7

Cylinder Type Cu. Ft. Liters

H 225 6371

M 111 3143

40 40 1133

E 24 680

D 15 425

B 5 142

C 9 255

PACKAGE LABEL

OXYGEN, REFRIGERATED LIQUID USP – UN1073

ALWAYS KEEP CONTAINER IN UPRIGHT POSITION
DO NOT CHANGE OR FORCE FIT CONNECTIONS.

WARNING:
For emergency use only when administered by properly trained personnel for oxygen deficiency and resuscitation. For all other medical applications, Rx required.
Uninterrupted use of high concentrations of oxygen over a long duration, without monitoring its effect on oxygen content of arterial blood, may be harmful. Do not attempt to use on patients who have stopped breathing unless used in conjunction with resuscitative equipment.
Produced by Air Liquefaction.

DANGER:
MAY CAUSE OR INTENSIFY FIRE; OXIDIZER. CONTAINS REFRIGERATED GAS; MAY CAUSE CRYOGENIC BURNS OR INJURY.
COMBUSTIBLES IN CONTACT WITH OXIDIZING REFRIGERATED GASES MAY EXPLODE ON IGNITION OR IMPACT.
Keep and store away from clothing and other combustible materials.
Keep valves and fittings free from grease and oil.
Use and store only outdoors or in a well-ventilated place.
In case of fire: Stop leak if safe to do so.
Use a back flow preventive device in the piping.
Use only with equipment of compatible materials of construction and rated for cylinder pressure.
Use only with equipment cleaned for oxygen service.
Close valve after each use and when empty.
Protect from sunlight when ambient temperature exceeds 52C (125F).
Read and follow the Safety Data Sheet (SDS) before use.

FIRST AID:
IF ON SKIN: Thaw frosted parts with lukewarm water. Do not rub affected area. Get immediate medical advice/attention.

CAS: 7782-44-7
DO NOT REMOVE THIS PRODUCT LABEL.

NO SMOKING / NO VAPING

American Welding & Gas, Inc.
4900 Falls of Neuse Road, Suite 150
Raleigh, NC 27609
800-967-6874

PACKAGE LABEL

OXYGEN, COMPRESSED USP – UN1072

WARNING:
For emergency use only when administered by properly trained personnel for oxygen deficiency and resuscitation. For all other medical applications, Rx required. Uninterrupted use of high concentrations of oxygen over a long duration, without monitoring its effect on oxygen content of arterial blood, may be harmful. Do not attempt to use on patients who have stopped breathing unless used in conjunction with resuscitative equipment.
Produced by Air Liquefaction.

DANGER:
MAY CAUSE OR INTENSIFY FIRE; OXIDIZER. CONTAINS GAS UNDER PRESSURE; MAY EXPLODE IF HEATED.
Obtain, read and follow all safety instructions before use. Keep away from clothing and other combustible materials. Keep valves and fittings free from grease and oil. Use and store only outdoors or in a well-ventilated place. Store in a well-ventilated place. In case of fire: Stop leak if safe to do so. Use a back flow preventive device in the piping. Use only with equipment of compatible materials of construction and rated for cylinder pressure. Use only with equipment cleaned for oxygen service. Do not open valve until connected to equipment prepared for use. Open valve slowly. Close valve after each use and when empty. Protect from sunlight when ambient temperature exceeds 52C (125F). Read and follow the Safety Data Sheet (SDS) before use.

NO SMOKING
NO VAPING

Coastal Welding Supply, Inc.
6026 Meaux St.
Beaumont, TX 77708
(409) 838-2511

American Welding & Gas, Inc.
4900 Falls of Neuse Road, Suite 150
Raleigh, NC 27609

CONTENTS:
LITERS CU.FT.

DO NOT REMOVE THIS PRODUCT LABEL.
CAS: 7782-44-7

PACKAGE LABEL

OXYGEN, REFRIGERATED LIQUID USP

UN1073
ALWAYS KEEP CONTAINER IN UPRIGHT POSITION
DO NOT CHANGE OR FORCE FIT CONNECTIONS.

WARNING:
For emergency use only when administered by properly trained personnel for oxygen deficiency and resuscitation.
For all other medical applications, Rx required.
Uninterrupted use of high concentrations of oxygen over a long duration, without monitoring its effect on oxygen content of arterial blood, may be harmful.
Do not attempt to use on patients who have stopped breathing unless used in conjunction with resuscitative equipment.
Produced by Air Liquefaction.

DANGER:
MAY CAUSE OR INTENSIFY FIRE; OXIDIZER.
CONTAINS REFRIGERATED GAS; MAY CAUSE CRYOGENIC BURNS OR INJURY.
COMBUSTIBLES IN CONTACT WITH OXIDIZING REFRIGERATED GASES MAY EXPLODE ON IGNITION OR IMPACT.
Keep and store away from clothing and other combustible materials.
Keep valves and fittings free from grease and oil.
Use and store only outdoors or in a well-ventilated place.
In case of fire: Stop leak if safe to do so.
Use a back flow preventive device in the piping.
Use only with equipment of compatible materials of construction and rated for cylinder pressure.
Use only with equipment cleaned for oxygen service.
Close valve after each use and when empty.
Protect from sunlight when ambient temperature exceeds 52C (125F).
Read and follow the Safety Data Sheet (SDS) before use.

FIRST AID:
IF ON SKIN: Thaw frosted parts with lukewarm water.
Do not rub affected area. Get immediate medical advice/attention.

CAS: 7782-44-7
DO NOT REMOVE THIS PRODUCT LABEL.

NO SMOKING / NO VAPING

Coastal Welding Supply, Inc.
6026 Meaux St.
Beaumont, TX 77708
(409) 838-2511

American Welding & Gas, Inc.
4900 Falls of Neuse Road, Suite 150
Raleigh, NC 27609